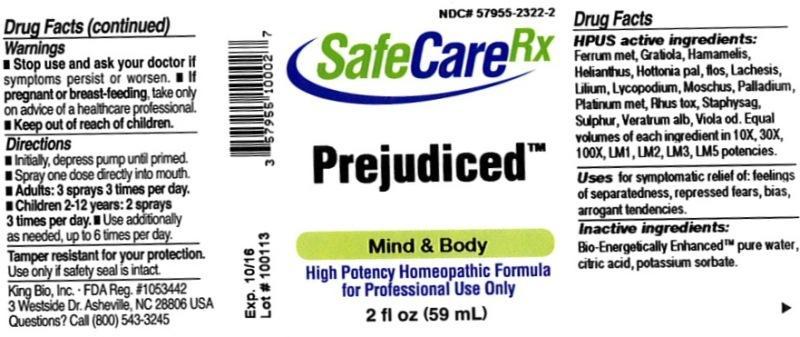 DRUG LABEL: Prejudiced
NDC: 57955-2322 | Form: LIQUID
Manufacturer: King Bio Inc.
Category: homeopathic | Type: HUMAN OTC DRUG LABEL
Date: 20131218

ACTIVE INGREDIENTS: IRON 10 [hp_X]/59 mL; GRATIOLA OFFICINALIS 10 [hp_X]/59 mL; HAMAMELIS VIRGINIANA ROOT BARK/STEM BARK 10 [hp_X]/59 mL; HELIANTHUS ANNUUS FLOWERING TOP 10 [hp_X]/59 mL; HOTTONIA PALUSTRIS FLOWER 10 [hp_X]/59 mL; LACHESIS MUTA VENOM 10 [hp_X]/59 mL; LILIUM LANCIFOLIUM WHOLE FLOWERING 10 [hp_X]/59 mL; LYCOPODIUM CLAVATUM SPORE 10 [hp_X]/59 mL; MOSCHUS MOSCHIFERUS MUSK SAC RESIN 10 [hp_X]/59 mL; PALLADIUM 10 [hp_X]/59 mL; PLATINUM 10 [hp_X]/59 mL; TOXICODENDRON PUBESCENS LEAF 10 [hp_X]/59 mL; DELPHINIUM STAPHISAGRIA SEED 10 [hp_X]/59 mL; SULFUR 10 [hp_X]/59 mL; VERATRUM ALBUM ROOT 10 [hp_X]/59 mL; VIOLA ODORATA 10 [hp_X]/59 mL
INACTIVE INGREDIENTS: WATER; CITRIC ACID MONOHYDRATE; POTASSIUM SORBATE

Prejudiced

Drug Facts

____________________________________________________________________________________________________________________

HPUS active ingredients: Ferrum metallicum, Gratiola officinalis, Hamamelis virginiana, Helianthus annuus, Hottonia palustris, flos, Lachesis mutus, Lilium tigrinum, Lycopodium clavatum, Moschus, Palladium metallicum, Platinum metallicum, Rhus toxicodendron, Staphysagria, Sulphur, Veratrum album, Viola odorata. Equal volumes of each ingredient in 10X, 30X, 100X, LM1, LM2, LM3, LM5 potencies.

INDICATIONS AND USAGE

Uses for symptomatic relief of: feelings of separatedness, repressed fears, bias, arrogant tendencies.

INACTIVE INGREDIENT

Inactive ingredients: Bio-Energetically Enhanced pure water, citric acid, potassium sorbate.

Warnings

- Stop use and ask your doctor if symptoms persist or worsen.
- If pregnant or breast-feeding, take only on advice of a healthcare professional.

- Keep out of reach of children.

Directions:

- Initially, depress pump until primed.
- Spray one dose directly into mouth.
- Adults: 3 sprays 3 times per day.
- Children 2-12 years: 2 sprays 3 times per day.
- Use addiitionally as needed, up to 6 times per day.

OTHER SAFETY INFORMATION

Tamper resistant for your protection. Use only if safety seal is intact.

PURPOSE

Uses for symptomatic relief of:

- feelings of separatedness
- repressed fears
- bias
- arrogant tendencies